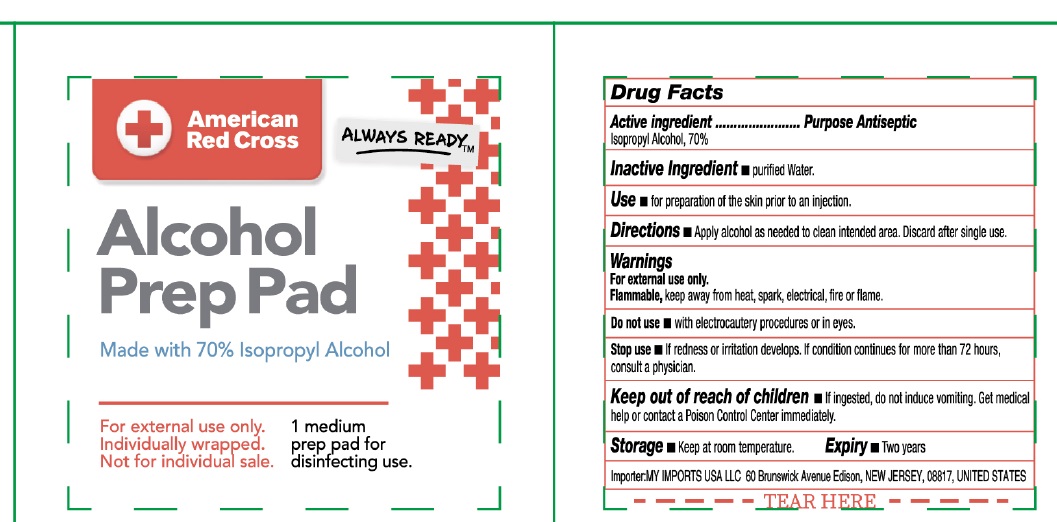 DRUG LABEL: American Red Cross Alcohol Prep Pad
NDC: 69139-011 | Form: SWAB
Manufacturer: YIWU HAODING MEDICAL CO.,LTD
Category: otc | Type: HUMAN OTC DRUG LABEL
Date: 20250430

ACTIVE INGREDIENTS: ISOPROPYL ALCOHOL 70 mL/100 mL
INACTIVE INGREDIENTS: WATER

69139-011 Alcohol prep pad

DRUG FACTS

Active Ingredient

Isopropyl Alcohol 70%

Purpose

Antiseptic

Uses:

For preparation of the skin prior to an injection

Use

Apply alcohol as needed to clean intended area. Discard after single use.

Warning

For external use only.

Flammable,keep away from heat, spark, electrical, fire, or flame.

Do not use:with electrocautery procedures or in eyes.

STOP USE

Stop useif redness or irritation develops. If condition persists for more than 72 hours, consult a physician.

Keep out of reach of children.

If swallowed, get medical help or contact a Poison Control Center right away.

Inactive Ingredients:

water